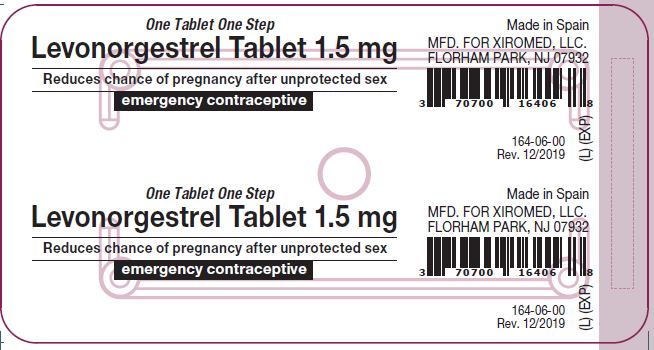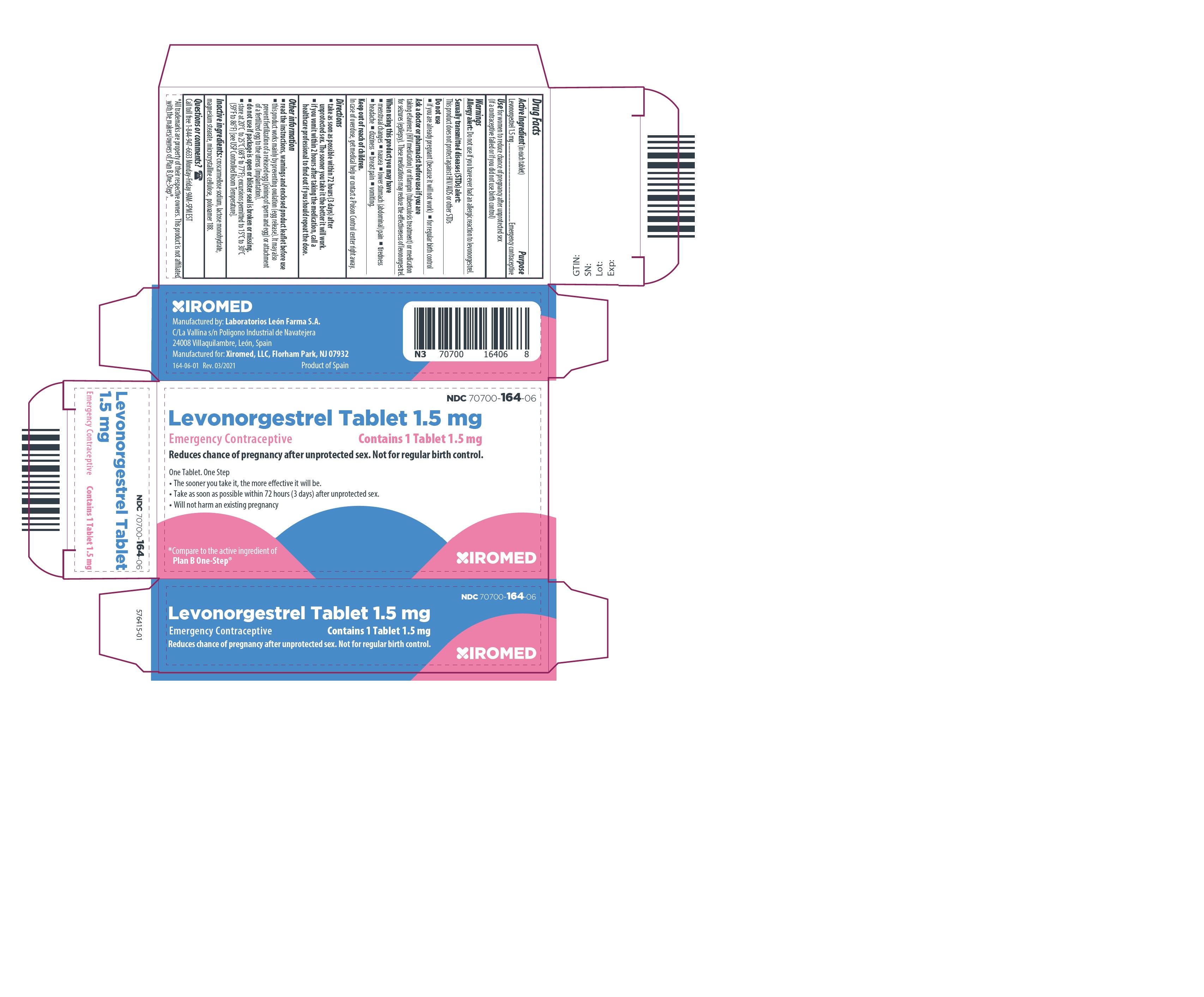 DRUG LABEL: Levonorgestrel
NDC: 70700-164 | Form: TABLET
Manufacturer: Xiromed LLC
Category: otc | Type: HUMAN OTC DRUG LABEL
Date: 20230905

ACTIVE INGREDIENTS: Levonorgestrel 1.5 mg/1 1
INACTIVE INGREDIENTS: Cellulose, Microcrystalline; Lactose Monohydrate; Croscarmellose Sodium; Poloxamer 188; Magnesium Stearate

Levonorgestrel Tablet 1.5 mg

Active ingredient

Levonorgestrel 1.5 mg

Purpose

Emergency contraceptive

Use

for women to reduce chance of pregnancy after unprotected sex (if a contraceptive failed or if you did not use birth control)

Warnings

Allergy alert: Do not use if you have ever had an allergic reaction to levonorgestrel

Sexually transmitted diseases (STDs) alert: This product does not protect against HIV/AIDS or other STDs

Do not use

- if you are already pregnant (because it will not work)
- for regular birth control

Ask a doctor or pharmacist before use if you are taking efavirenz (HIV medication) or rifampin (tuberculosis treatment) or medication for seizures (epilepsy). These medications may reduce the effectiveness of levonorgestrel.

When using this product you may have

• menstrual changes

• tiredness

• breast pain

• nausea

• headache

• vomiting

• lower stomach (abdominal) pain

• dizziness

Keep out of reach of children.

In case of overdose, get medical help or contact a Poison Control center right away.

Directions

- take as soon as possible within 72 hours (3 days) after unprotected sex. The sooner you take it the better it will work.
- if you vomit within 2 hours after taking the medication, call a healthcare professional to find out if you should repeat the dose

Other information

- read the instructions, warnings and enclosed product leaflet before use
- do not use if carton is open or blister seal is broken or missing
- store at 20–25°C (68–77°F)

Inactive ingredients

croscarmellose sodium, lactose monohydrate, magnesium stearate, microcrystalline cellulose, poloxamer 188

Questions?

Call 1-844-947-6633 Monday-Friday 9AM-5PM EST

What is levonorgestrel tablet 1.5 mg?

Levonorgestrel tablet 1.5 mg is emergency contraception that helps prevent pregnancy after birth control failure or unprotected sex. It is a backup method of preventing pregnancy and should not be used as regular birth control.

What levonorgestrel tablet 1.5 mg is not.

Levonorgestrel tablet 1.5 mg will not work if you are already pregnant and will not affect an existing pregnancy. Levonorgestrel tablet 1.5 mg will not protect you from HIV infection (the virus that causes AIDS) and other sexually transmitted diseases (STDs).

When should I use levonorgestrel tablet 1.5 mg?

The sooner you take emergency contraception, the better it works. You should use levonorgestrel tablet 1.5 mg within 72 hours (3 days) after you have had unprotected sex.

Levonorgestrel tablet 1.5 mg is a backup or emergency method of birth control you can use when:

1. your regular birth control was used incorrectly or failed
2. you did not use any birth control method

When not to use levonorgestrel tablet 1.5 mg.

Levonorgestrel tablet 1.5 mg should not be used:

1. as a regular birth control method, because it’s not as effective as regular birth control.
2. if you are already pregnant, because it will not work.
3. if you are allergic to levonorgestrel or any other ingredients in levonorgestrel tablet 1.5 mg.

When should I talk to a doctor or pharmacist?

Ask a doctor or pharmacist before use if you are taking efavirenz (HIV medication) or rifampin (tuberculosis treatment) or medication for seizures (epilepsy). These medications may reduce the effectiveness of levonorgestrel tablet and increase your chance of becoming pregnant. Your doctor may prescribe another form of emergency contraception that may not be affected by these medications.

How does levonorgestrel tablet 1.5 mg work?

Levonorgestrel tablet 1.5 mg works before release of an egg from the ovary. As a result, levonorgestrel tablet usually stops or delays the release of an egg from the ovary. Levonorgestrel tablet is one tablet that contains a higher dose of levonorgestrel than birth control pills and works in a similar way to prevent pregnancy.

How can I get the best results from levonorgestrel tablet 1.5 mg?

You have 72 hours (3 days) to try to prevent pregnancy after birth control failure or unprotected sex. The sooner you take levonorgestrel tablet 1.5 mg, the better it works.

How effective is levonorgestrel tablet 1.5 mg?

If levonorgestrel tablet 1.5 mg is taken as directed, it can significantly decrease the chance that you will get pregnant. About 7 out of every 8 women who would have gotten pregnant will not become pregnant.

How will I know levonorgestrel tablet 1.5 mg worked?

You will know levonorgestrel tablet 1.5 mg has been effective when you get your next period, which should come at the expected time, or within a week of the expected time. If your period is delayed beyond 1 week, it is possible you may be pregnant. You should get a pregnancy test and follow up with your healthcare professional.

Will I experience any side effects?

1. some women may have changes in their period, such as a period that is heavier or lighter or a period that is early or late. If your period is more than a week late, you may be pregnant.
2. if you have severe abdominal pain, you may have an ectopic pregnancy, and should get immediate medical attention.
3. when used as directed, levonorgestrel tablet 1.5 mg is safe and effective. Side effects may include changes in your period, nausea, lower stomach (abdominal) pain, tiredness, headache, dizziness, and breast tenderness.
4. if you vomit within 2 hours of taking the medication, call a healthcare professional to find out if you should repeat the dose.

What if I still have questions about levonorgestrel tablet 1.5 mg?

If you have questions or need more information, call our toll-free number, 1-844-947-6633, or visit our website at www.xiromed.com.

Keep out of reach of children:

In case of overdose, get medical help or contact a Poison Control Center right away at 1-800-222-1222.

STORAGE AND HANDLING

Store at 20–25°C (68–77°F)

Active ingredient: levonorgestrel 1.5 mg

Inactive ingredients: croscarmellose sodium, lactose monohydrate, magnesium stearate, microcrystalline cellulose, poloxamer 188

1-844-947-6633

www.xiromed.com

If you are sexually active, you should see a healthcare provider for routine checkups. Your healthcare provider will talk to you about and, if necessary, test you for sexually transmitted diseases, teach you about effective methods of routine birth control, and answer any other questions you may have.

XIROMED, LLC.
Levonorgestrel tablet 1.5 mg

Manufactured by:
Laboratorios León Farma S.A.
C/La Vallina s/n
Poligono Industrial de
Navatejera
24008 Villaquilambre, León,
Spain
Manufactured for:
Xiromed, LLC.
Florham Park, NJ 07932

164-06-01 Rev. 09/2023

Principle Display Panel - Carton

Levonorgestrel Tablet
(levonorgestrel) tablet 1.5 mg
Emergency contraceptive
Reduces chance of pregnancy after unprotected sex.
Not for regular birth control.
Xiromed LLC.